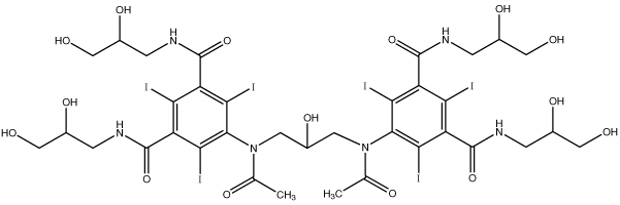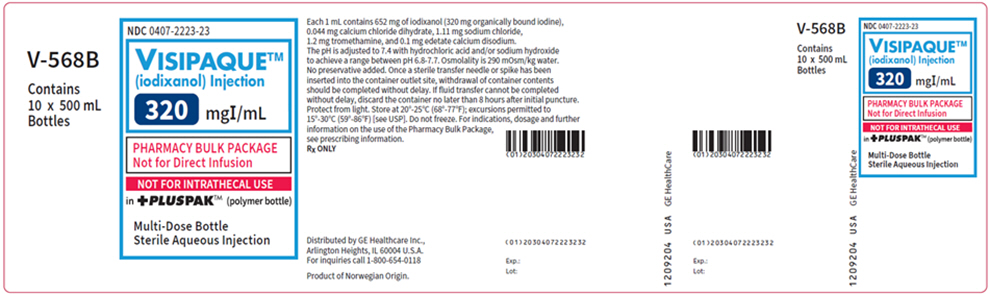 DRUG LABEL: Visipaque
NDC: 0407-2223 | Form: INJECTION, SOLUTION
Manufacturer: GE Healthcare Inc.
Category: prescription | Type: HUMAN PRESCRIPTION DRUG LABEL
Date: 20251017

ACTIVE INGREDIENTS: Iodixanol 320 mg/1 mL
INACTIVE INGREDIENTS: Calcium Chloride 0.044 mg/1 mL; Sodium Chloride 1.11 mg/1 mL; Tromethamine 1.2 mg/1 mL; Edetate Calcium Disodium 0.1 mg/1 mL

HIGHLIGHTS OF PRESCRIBING INFORMATION

These highlights do not include all the information needed to use VISIPAQUE safely and effectively. See full prescribing information for VISIPAQUE.
VISIPAQUE (iodixanol) injection, for intra-arterial or intra-venous use
Initial U.S. Approval: 1996
PHARMACY BULK PACKAGE- NOT FOR DIRECT INFUSION

WARNING: NOT FOR INTRATHECAL USE

See full prescribing information for complete boxed warning

Inadvertent intrathecal administration may cause death, convulsions/seizures, cerebral hemorrhage, coma, paralysis, arachnoiditis, acute renal failure, cardiac arrest, rhabdomyolysis, hyperthermia, and brain edema. (4, 5.1)

1 INDICATIONS AND USAGE

VISIPAQUE injection is a radiographic contrast agent indicated for the following:

Intra-arterial Procedures (1.1)

Adults and pediatric patients 12 years of age and over

- Intra-arterial digital subtraction angiography (270 and 320 mg Iodine/mL).
- Angiocardiography (left ventriculography and selective coronary arteriography), peripheral arteriography, visceral arteriography, and cerebral arteriography (320 mg Iodine/mL).

Pediatric patients less than 12 years of age

- Angiocardiography, cerebral arteriography, and visceral arteriography (320 mg Iodine/mL).

Intravenous Procedures (1.2)

Adults and pediatric patients 12 years of age and over

- Computed tomography (CT) imaging head and body (270 and 320 mg Iodine/mL).
- Excretory urography (270 and 320 mg Iodine/mL).
- Peripheral venography (270 mg Iodine/mL).
- Coronary computed tomography angiography (CCTA) to assist diagnostic evaluation of patients with suspected coronary artery disease (320 mg Iodine/mL).

Pediatric patients less than 12 years of age

- CT imaging of the head and body (270 mg Iodine/mL).
- Excretory urography (270 mg Iodine/mL).

2 DOSAGE AND ADMINISTRATION

- Individualize the combination of volume and concentration of VISIPAQUE Injection considering age, body weight, size of the vessel, rate of blood flow within the vessel, and other applicable factors. (2.1, 2.2, 2.3, 2.4)
- For the adult patients, the maximum recommended total dose of iodine is 80 grams. (2.1)
- Patients should be adequately hydrated prior to and following the intravascular administration of iodinated contrast agents. (2.1, 5.3)

3 DOSAGE FORMS AND STRENGTHS

Injection: In concentrations of 270 and 320 mg of organically bound iodine per mL (550 mg and 652 mg of Iodixanol per mL). (3)

4 CONTRAINDICATIONS

- Not indicated for intrathecal use. (4)

5 WARNINGS AND PRECAUTIONS

- Hypersensitivity Reactions: Life-threatening or fatal reactions can occur. Always have emergency equipment and trained personnel available. (5.2)
- Contrast-Induced Acute Kidney Injury: Acute injury including renal failure can occur. Minimize dose and maintain adequate hydration to minimize risk. (5.3)
- Cardiovascular reactions: Hemodynamic disturbances including shock and cardiac arrest may occur during or after administration. (5.4)
- Thyroid dysfunction in pediatric patients 0 to 3 Years of Age: Individualize thyroid function monitoring based on risk factors such as prematurity. (5.8)

6 ADVERSE REACTIONS

Most common adverse reactions (incidence greater than 0.5%) in adult patients after VISIPAQUE injection: Discomfort, warmth, pain; Cardiovascular: angina. Gastrointestinal: diarrhea, nausea, vomiting. Nervous System: agitation, anxiety, insomnia, nervousness, dizziness, headache, migraine, unusual skin sensations, sensory disturbance, fainting, sensation of spinning. Skin: itchy rash, severe itching, hives. Special Senses: Smell, taste, and vision alteration. (6.1) Pediatric patients experienced similar adverse reactions. (6.3)

To report SUSPECTED ADVERSE REACTIONS, contact GE HealthCare at 1-800-654-0118 or FDA at 1-800-FDA-1088 or www.fda.gov/medwatch.

8 USE IN SPECIFIC POPULATIONS

- Lactation: A lactating woman may pump and discard breast milk for 10 hours after VISIPAQUE administration. (8.2)
- Geriatrics: Exercise caution in dose selection for elderly patients. (8.5)

FULL PRESCRIBING INFORMATION

WARNING: NOT FOR INTRATHECAL USE

Inadvertent intrathecal administration may cause death, convulsions/seizures, cerebral hemorrhage, coma, paralysis, arachnoiditis, acute renal failure, cardiac arrest, rhabdomyolysis, hyperthermia, and brain edema [see Contraindications (4) and Warnings and Precautions (5.1)].

1 INDICATIONS AND USAGE

VISIPAQUE is indicated for:

1.1 Intra-arterial Procedures

Adult and pediatric patients 12 years of age and older

- (270 and 320 mg Iodine/mL) intra-arterial digital subtraction angiography (IA-DSA).
- (320 mg Iodine/mL) angiocardiography (left ventriculography and selective coronary arteriography), peripheral arteriography, visceral arteriography, and cerebral arteriography.

Pediatric patients less than 12 years of age

- (320 mg Iodine/mL) angiocardiography, cerebral arteriography, and visceral arteriography.

1.2 Intravenous Procedures

Adult and pediatric patients 12 years of age and older

- (270 and 320 mg Iodine/mL) CT imaging of the head and body.
- (270 and 320 mg Iodine/mL) excretory urography.
- (270 mg Iodine/mL) peripheral venography.
- (320 mg Iodine/mL) coronary computed tomography angiography (CCTA) to assist in the diagnostic evaluation of patients with suspected coronary artery disease.

Pediatric patients less than 12 years of age

- (270 mg Iodine/mL) CT imaging of the head and body.
- (270 mg Iodine/mL) excretory urography.

2 DOSAGE AND ADMINISTRATION

2.1 Important Dosage and Administration Instructions

- VISIPAQUE is for intravascular use only [see Boxed Warning, Contraindications (4), and Warnings and Precautions (5.1)]
- Use sterile technique for all handling and administration of VISIPAQUE.
- Do not use if tamper-evident ring is broken or missing.
- Warm VISIPAQUE and administer at body or room temperature.
- Inspect VISIPAQUE for particulate matter or discoloration before administration, whenever solution and container permit. Do not administer if VISIPAQUE contains particulate matter or is discolored.
- Do not mix VISIPAQUE with, or inject in intravenous lines containing, other drugs or total nutritional admixtures.
- Use the lowest dose necessary to obtain adequate visualization.
- Individualize the volume, strength, and rate of administration of VISIPAQUE. Consider factors such as age, bodyweight, vessel size, blood flow rate within the vessel, anticipated pathology, degree and extent of opacification required, structures or area to be examined, disease processes affecting the patient, and equipment and technique to be employed.
- The maximum recommended total dose of iodine for adults is 80 grams.
- Avoid extravasation when injecting VISIPAQUE; especially in patients with severe arterial or venous disease [see Warnings and Precautions (5.6)].
- Hydrate patients before and after VISIPAQUE administration [see Warnings and Precautions (5.3)].

2.2 Intra-Arterial Dosage and Administration

- Intra-arterial digital subtraction angiography (IA-DSA) (270 and 320 mg Iodine/mL)
- Angiocardiography (left ventriculography and selective coronary arteriography), peripheral arteriography, visceral arteriography, and cerebral arteriography (320 mg Iodine/mL)

Use Injection rates approximately equal to the flow rate in the vessel being injected. The usual single injection volumes or total dose per patient (mL/kg) for adults and adolescents over 12 years of age are listed in Table 1.

TABLE 1 ADULTS and PEDIATRIC PATIENTS 12 YEARS OF AGE AND OLDER VISIPAQUE SINGLE DOSE RECOMMENDATIONS FOR INJECTION INTO SELECTED ARTERIES
 | ARTERIOGRAPHY | IA-DSA [IA-DSA = Intra-Arterial Digital Subtraction Angiography]
Intra-Arterial Injection Sites | 320 mg Iodine/mL | 270 mg Iodine/mL | 320 mg Iodine/mL | Maximum Total Dose
Carotid Arteries | 10 to 14 mL |  | 5 to 8 mL | Usually Not to Exceed 175 mL
Vertebral Arteries | 10 to 12 mL |  | 5 to 8 mL | Usually Not to Exceed 175 mL
Right Coronary Artery | 3 to 8 mL |  |  | Usually Not to Exceed 200 mL
Left Coronary Artery | 3 to 10 mL |  |  | Usually Not to Exceed 200 mL
Left Ventricle | 20 to 45 mL |  |  | Usually Not to Exceed 200 mL
Renal Arteries | 8 to 18 mL | 10 to 25 mL | -- | Usually Not to Exceed 250 mL
Aortography | 30 to 70 mL | 20 to 50 mL | 10 to 50 mL | Usually Not to Exceed 250 mL
Major Branches of Aorta | 10 to 70 mL | 5 to 30 mL | 2 to 10 mL | Usually Not to Exceed 250 mL
Aortofemoral Runoffs | 20 to 90 mL | -- | 6 to 15 mL | Usually Not to Exceed 250 mL
Peripheral Arteries | 15 to 30 mL | -- | 3 to 15 mL | Usually Not to Exceed 250 mL

2.3 Intravenous Dosage and Administration

- Computed Tomography of the Head or Body (270 mg Iodine/mL and 320 mg Iodine/mL)
- Excretory Urography (270 mg Iodine/mL and 320 mg Iodine/mL)
- Peripheral Venography (270 mg Iodine/mL)
- Coronary Computed Tomography Angiography (CCTA) (320 mg Iodine/mL)

Recommended dosage of VISIPAQUE is dependent on: the administration procedure, patient weight, and CT device factors, as detailed in Table 2.Calibrate the intravenous injection rate so that image acquisition coincides with peak arterial concentration. The time between VISIPAQUE injection and peak arterial concentration varies between patients. Selected dosing for different indications in adults and pediatric patients over 12 years of age are shown in Table 2.

TABLE 2 ADULTS and PEDIATRIC PATIENTS 12 YEARS OF AGE AND OLDER VISIPAQUE DOSING RECOMMENDATIONS FOR INTRAVENOUS CONTRAST ADMINISTRATION
Study Type | Comment | 270 mg Iodine/mL | 320 mg Iodine/mL | Maximum Total Volume
CT of Head or Body | Bolus Infusion | 75 to 150 mL 100 to 150 mL | 75 to 150 mL 100 to 150 mL | 150 mL
Excretory Urography | Normal Renal Function | 1 mL/kg | 1 mL/kg | 100 mL
Venography | Per lower extremity | 50 to 150 mL |  | 250 mL
CCTA [For pediatric patients aged 12 to 17, recommended dose is 1 to 2 mL/kg.] | Bolus injection with test bolus [The main VISIPAQUE volume may be preceded by a test bolus consisting of 20 mL VISIPAQUE, immediately followed by a 20 mL saline flush, both injected at rate of 4 to 7 mL/sec.] or bolus tracking |  | 50 to 150 mL [Injection of VISIPAQUE with saline can be either biphasic (without dilution phase) or triphasic (with dilution phase). Alternatively, a dose of 1 mL/kg may be used to calculate total VISIPAQUE dose (excluding any test bolus). For CCTA acquired at < 120 kVp, the dose of VISIPAQUE may be reduced by up to 15% in patients < 85 kg and BMI < 30 kg/m^2. For CCTA acquired on a scanner with more than 64 detector rows, the dose of VISIPAQUE may be reduced in proportion to the scan duration.] (4 to 7 mL per second) | 150 mL

2.4 Dosage in Pediatric Patients Less Than 12 Years of Age

Intra-arterial Dosage and Administration

Angiocardiography, cerebral arteriography, or visceral arteriography (320 mg Iodine/mL):

The recommended dosage is 1 to 2 mL/kg. The maximum dose should not exceed 4 mL/kg.

Intravenous Dosage and Administration

Computerized Tomography or Excretory Urography (270 mg Iodine/mL):

The recommended dosage is 1 to 2 mL/kg. The maximum dose should not exceed 2 mL/kg.

3 DOSAGE FORMS AND STRENGTHS

Injection: Non-ionic, isotonic, water-soluble, sterile, pyrogen-free, colorless to pale yellow solution in the following strengths:

- 270 mg of organically bound iodine per mL (550 mg Iodixanol per mL).
- 320 mg of organically bound iodine per mL (652 mg Iodixanol per mL).

Available in the following formats: Multiple-dose polymer bottle (+PLUSPAK™) and Single-dose polymer bottle (+PLUSPAK™).

4 CONTRAINDICATIONS

VISIPAQUE is contraindicated for Intrathecal use [see Warnings and Precautions (5.1)].

5 WARNINGS AND PRECAUTIONS

5.1 Risks Associated with Inadvertent Intrathecal Administration

VISIPAQUE is for intravascular use only and is contraindicated for intrathecal use [see Contraindications (4) and Dosage and Administration (2.1)]. Inadvertent Intrathecal administration can cause death, convulsions/seizures, cerebral hemorrhage, coma, paralysis, arachnoiditis, acute renal failure, cardiac arrest, rhabdomyolysis, hyperthermia, and brain edema.

5.2 Hypersensitivity Reactions

VISIPAQUE can cause life-threatening or fatal hypersensitivity reactions including anaphylaxis. Manifestations include respiratory arrest, laryngospasm, bronchospasm, angioedema, and shock. Most severe reactions develop shortly after the start of the injection (within 3 minutes), but reactions can occur up to hours later. There is an increased risk in patients with a history of a previous reaction to contrast agent, and known allergies (i.e., bronchial asthma, drug, or food allergies) or other hypersensitivities. Premedication with antihistamines or corticosteroids does not prevent serious life-threatening reactions, but may reduce both their incidence and severity.

Obtain a history of allergy, hypersensitivity, or hypersensitivity reactions to iodinated contrast agents and always have emergency resuscitation equipment and trained personnel available prior to VISIPAQUE administration. Monitor all patients for hypersensitivity reactions.

5.3 Contrast-Induced Acute Kidney Injury

Acute kidney injury, including renal failure, may occur after VISIPAQUE administration. Risk factors include: pre-existing renal impairment, dehydration, diabetes mellitus, congestive heart failure, advanced vascular disease, elderly age, concomitant use of nephrotoxic or diuretic medications, multiple myeloma/paraproteinaceous diseases, repetitive and/or large doses of an iodinated contrast agent.

Use the lowest necessary dose of VISIPAQUE in patients with renal impairment. Adequately hydrate patients prior to and following VISIPAQUE administration. Do not use laxatives, diuretics, or preparatory dehydration prior to VISIPAQUE administration.

5.4 Cardiovascular Adverse Reactions

Life-threatening or fatal cardiovascular reactions including hypotension, shock, cardiac arrest have occurred with the use of VISIPAQUE. Most deaths occur during injection or five to ten minutes later, with cardiovascular disease as the main aggravating factor. Cardiac decompensation, serious arrhythmias, and myocardial ischemia or infarction can occur during coronary arteriography and ventriculography.

Based upon clinical literature reported deaths from the administration of iodinated contrast agents range from 6.6 per million (0.00066%) to 1 in 10,000 (0.01%). Use the lowest necessary dose of VISIPAQUE in patients with congestive heart failure and always have emergency resuscitation equipment and trained personnel available. Monitor all patients for severe cardiovascular reactions.

5.5 Thromboembolic Events

Angiocardiography

Serious, rarely fatal, thromboembolic events causing myocardial infarction and stroke can occur during angiocardiography procedures with both ionic and nonionic contrast media. During these procedures, increased thrombosis and activation of the complement system occurs. Risk factors for thromboembolic events include: length of procedure, catheter and syringe material, underlying disease state, and concomitant medications.

To minimize thromboembolic events, use meticulous angiographic techniques, and minimize the length of the procedure. Avoid blood remaining in contact with syringes containing iodinated contrast agents, which increases the risk of clotting. Avoid angiocardiography in patients with homocystinuria because of the risk of inducing thrombosis and embolism.

5.6 Extravasation and Injection Site Reactions

Extravasation of VISIPAQUE Injection may cause tissue necrosis and/or compartment syndrome, particularly in patients with severe arterial or venous disease. Ensure intravascular placement of catheters prior to injection. Monitor patients for extravasation and advise patients to seek medical care for progression of symptoms.

5.7 Thyroid Storm in Patients with Hyperthyroidism

Thyroid storm has occurred after the intravascular use of iodinated contrast agents in patients with hyperthyroidism, or with an autonomously functioning thyroid nodule. Evaluate the risk in such patients before use of VISIPAQUE.

5.8 Thyroid Dysfunction in Pediatric Patients 0 to 3 Years of Age

Thyroid dysfunction characterized by hypothyroidism or transient thyroid suppression has been reported after both single exposure and multiple exposures to iodinated contrast media (ICM) in pediatric patients 0 to 3 years of age.

Younger age, very low birth weight, prematurity, underlying medical conditions affecting thyroid function, admission to neonatal or pediatric intensive care units, and congenital cardiac conditions are associated with an increased risk of hypothyroidism after ICM exposure. Pediatric patients with congenital cardiac conditions may be at the greatest risk given that they often require high doses of contrast during invasive cardiac procedures.

An underactive thyroid during early life may be harmful for cognitive and neurological development and may require thyroid hormone replacement therapy. After exposure to ICM, individualize thyroid function monitoring based on underlying risk factors, especially in term and preterm neonates.

5.9 Hypertensive Crisis in Patients with Pheochromocytoma

Hypertensive crisis has occurred after the use of iodinated contrast agents in patient with pheochromocytoma. Monitor patients when administering VISIPAQUE if pheochromocytoma or catecholamine-secreting paragangliomas are suspected. Inject the minimum amount of contrast necessary, assess the blood pressure throughout the procedure, and have measures for treatment of a hypertensive crisis readily available.

5.10 Sickle Cell Crisis in Patients with Sickle Cell Disease

Iodinated contrast agents when administered intravascularly may promote sickling in individuals who are homozygous for sickle cell disease. Hydrate patients prior to and following VISIPAQUE administration and use VISIPAQUE only if the necessary imaging information cannot be obtained with alternative imaging modalities.

5.11 Severe Cutaneous Adverse Reactions

Severe cutaneous adverse reactions (SCAR) may develop from 1 hour to several weeks after intravascular contrast agent administration. These reactions include Stevens-Johnson syndrome and toxic epidermal necrolysis (SJS/TEN), acute generalized exanthematous pustulosis (AGEP) and drug reaction with eosinophilia and systemic symptoms (DRESS).

Reaction severity may increase and time to onset may decrease with repeat administration of contrast agents; prophylactic medications may not prevent or mitigate severe cutaneous adverse reactions. Avoid administering VISIPAQUE to patients with a history of a severe cutaneous adverse reaction to VISIPAQUE.

6 ADVERSE REACTIONS

The following clinically significant adverse reactions are described elsewhere in the labeling:

- Risks Associated with Inadvertent Intrathecal Administration [see Warnings and Precautions (5.1)]
- Hypersensitivity Reactions [see Warnings and Precautions (5.2)]
- Contrast-Induced Kidney Injury [see Warnings and Precautions (5.3)]
- Cardiovascular Adverse Reactions [see Warnings and Precautions (5.4)]
- Thromboembolic Events [see Warnings and Precautions (5.5)]
- Thyroid Dysfunction in Pediatric Patients 0 to 3 Years of Age [see Warnings and Precautions (5.8)]
- Severe Cutaneous Adverse Reactions [see Warnings and Precautions (5.11)]

6.1 Clinical Trials Experience

Because clinical trials are conducted under widely varying conditions, adverse reaction rates observed in the clinical trials of a drug cannot be directly compared to rates in the clinical trials of another drug and may not reflect the rates observed in practice.

VISIPAQUE is often associated with sensations of discomfort, warmth or pain. In a subgroup of 1259 patients; 30% who received VISIPAQUE or a comparator had application site discomfort, pain, warmth or cold. VISIPAQUE had a trend toward fewer patient reports of moderate or severe pain or warmth. Pain was reported in 2% of patients receiving VISIPAQUE and 10% of patients receiving a comparator. Heat was reported in 29% of patients receiving VISIPAQUE and 51% of patients receiving a comparator.

Table 3 shows the incidence of events reported in blinded, controlled clinical studies of VISIPAQUE in a total of 1244 adult patients. Adverse events (AEs) are listed by body system and in decreasing order of occurrence greater than 0.5% of patients. One or more adverse events were reported in 20% of patients during the study period (24 to 72 hours). In a 757 patient subgroup, the number of women reporting adverse events was 83/299 (28%) and the number of men was 77/458 (16%). A total of 3% of women and 0.8% of men reported chest pain.

TABLE 3 ADVERSE EVENTS REPORTED IN CONTROLLED CLINICAL TRIALS IN GREATER THAN 0.5% OF 1244 ADULT PATIENTS RECEIVING VISIPAQUE OR OTHER IODINATED CONTRAST AGENTS
NUMBER OF PATIENTS EXPOSED |  | VISIPAQUE N (%) = 1244 | Pooled Comparators N (%) = 861
Number of Patients with Any Adverse Event |  | 248 (19.9) | 194 (22.5)
Body As a Whole | Patients with Any Event | 41 (3.3) | 22 (2.6)
Body As a Whole | Edema (any location) | 7 (0.6) | 0 (0)
Cardiovascular | Patients with Any Event | 37 (3.0) | 39 (4.5)
Cardiovascular | Angina Pectoris/Chest Pain | 28 (2.2) | 22 (2.6)
Gastrointestinal | Patients with Any Event | 51 (4.1) | 46 (5.3)
Gastrointestinal | Diarrhea | 7 (0.6) | 6 (0.7)
Gastrointestinal | Nausea | 35 (2.8) | 32 (3.7)
Gastrointestinal | Vomiting | 10 (0.8) | 11 (1.3)
Nervous System | Patients with Any Event | 101 (8.1) | 60 (7.0)
Nervous System | Agitation, Anxiety, Insomnia, Nervousness | 10 (0.8) | 0 (0)
Nervous System | Dizziness | 8 (0.7) | 8 (0.9)
Nervous System | Headache/Migraine | 31 (2.5) | 15 (1.7)
Nervous System | Paresthesia | 12 (1.0) | 1 (0.1)
Nervous System | Sensory Disturbance | 10 (0.8) | 9 (1.0)
Nervous System | Syncope | 8 (0.6) | 1 (0.1)
Nervous System | Vertigo | 30 (2.4) | 20 (2.3)
Skin (not including application site) | Patients with Any Event | 42 (4.6) | 18 (2.1)
Skin (not including application site) | Nonurticarial Rash or Erythema | 26 (2.1) | 4 (0.5)
Skin (not including application site) | Pruritus | 20 (1.6) | 3 (0.3)
Skin (not including application site) | Urticaria | 6 (0.5) | 10 (1.2)
Special Senses | Patients with Any Event | 57 (4.6) | 38 (4.4)
Special Senses | Parosmia | 6 (0.5) | 4 (0.5)
Special Senses | Taste Perversion | 43 (3.5) | 32 (3.7)
Special Senses | Scotoma | 14 (1.1) | 2 (0.2)

The following selected adverse events were reported in ≤0.5% of the 1244 patients.

Body as a Whole—General Disorders: back pain, fatigue, malaise

Cardiovascular Disorders: arrhythmias, cardiac failure, conduction abnormalities, hypotension, myocardial infarction

Gastrointestinal System Disorders: dyspepsia

Hypersensitivity Disorders: pharyngeal edema

Nervous System: cerebral vascular disorder, convulsions, hypoesthesia, stupor, confusion

Peripheral Vascular Disorders: flushing, peripheral ischemia

Renal System Disorders: abnormal renal function, acute renal failure, hematuria

Respiratory System Disorders: asthma, bronchitis, dyspnea, pulmonary edema, rhinitis

Skin and Appendage Disorders: hematoma, increased sweating

Special Senses, Other Disorders: tinnitus

Vision Disorders: abnormal vision

6.2 Post-marketing Experience

The following additional adverse reactions have been identified during post approval use of VISIPAQUE. Because these reactions are reported voluntarily from a population of uncertain size, it is not always possible to reliably estimate their frequency or establish a causal relationship to exposure.

Cardiovascular Disorders: Cardiac arrest, palpitations, spasms of coronary arteries, hypertension, and flushing

Endocrine Disorders: Hyperthyroidism, hypothyroidism

Eye Disorders: Transient visual impairment including cortical blindness, diplopia, and blurred vision

Gastrointestinal Disorders: Abdominal pain, pancreatitis, salivary gland enlargement

General Disorders and Administration Site Conditions: Chills, pyrexia, pain and discomfort, administration site reactions including extravasation

Immune System Disorders: Hypersensitivity reactions, anaphylactic shock including, life-threatening or fatal anaphylaxis

Nervous System Disorders: Tremor (transient), coma, disturbance in consciousness, transient contrast-induced encephalopathy caused by extravasation of contrast media (including amnesia, hallucination, paralysis, paresis, transient speech disorder, aphasia, dysarthria)

Psychiatric Disorders: Anxiety, agitation

Respiratory, Thoracic, and Mediastinal Disorders: Cough, sneezing, throat irritation or tightness, laryngeal edema, pharyngeal edema, bronchospasm

Skin and subcutaneous tissue disorders: Reactions range from mild (e.g., rash, erythema, pruritus, urticaria, and skin discoloration) to severe: [e.g., Stevens-Johnson syndrome and toxic epidermal necrolysis (SJS/TEN), acute generalized exanthematous pustulosis (AGEP) and drug reaction with eosinophilia and systemic symptoms (DRESS)]

6.3 Pediatric Adverse Reactions

The overall character, quality, and severity of adverse reactions in pediatric patients is similar to that reported in adult patients from post marketing surveillance and other information.

Additional safety data was obtained in studies of VISIPAQUE in 459 pediatric patients. A total of 26 patients ranged in age from birth to <29 days, 148 ranged from 29 days to 2 years, 263 from 2 to <12 years, and 22 from 12 to 18 years. A total of 252 (55%) of the patients were male. The racial distribution was: Caucasian-81%, Black-14%, Oriental-2%, and other or unknown-4%. The proportion of patients undergoing an intra-arterial procedure by age was: 92% (<29 days), 55% (29 days to 6 months), and 29% (>6 months). In these studies, adverse events were numerically higher in pediatric patients less than one year of age compared to older pediatric patients.

In pediatric patients who received intravenous injections of VISIPAQUE for computerized tomography or excretory urography, a concentration of 270 mg Iodine/mL was used in 144 patients, and a concentration of 320 mg Iodine/mL in 154 patients. All patients received one intravenous injection of 1 to 2 mL/kg.

In pediatric patients who received intra-arterial and intracardiac studies, a concentration of 320 mg Iodine/mL was used in 161 patients. Twenty-two patients were < 29 days of age; 78 were 29 days to 2 years of age; and 61 were over 2 years. Most of these pediatric patients received initial volumes of 1 to 2 mL/kg and most patients received a maximum of 3 injections.

7 DRUG INTERACTIONS

7.1 Drug-Drug Interactions

Metformin

In patients with renal impairment, metformin can cause lactic acidosis. Iodinated contrast agents appear to increase the risk of metformin-induced lactic acidosis, possibly as a result of worsening renal function. Stop metformin at the time of, or prior to, VISIPAQUE administration in patients with an eGFR between 30 and 60 mL/min/1.73 m^2; in patients with a history of hepatic impairment, alcoholism or heart failure; or in patients who will be administered intra-arterial iodinated contrast. Re-evaluate eGFR 48 hours after the imaging procedure, and reinstitute metformin only after renal function is stable.

Radioactive Iodine

Administration of iodinated contrast agents may interfere with thyroid uptake of radioactive iodine (I-131 and I-123) and decrease therapeutic and diagnostic efficacy in patients with carcinoma of the thyroid. The decrease in efficacy lasts for 6 to 8 weeks.

Beta-adrenergic Blocking Agents

The use of beta-adrenergic blocking agents lowers the threshold for and increases the severity of contrast reactions, and reduces the responsiveness of treatment of hypersensitivity reactions with epinephrine. Because of the risk of hypersensitivity reactions, use caution when administering VISIPAQUE to patients taking beta-blockers.

Oral Cholecystographic Contrast Agents

Renal toxicity has been reported in patients with liver dysfunction who were given an oral cholecystographic agent followed by intravascular iodinated contrast agents. Postpone the administration of VISIPAQUE in patients who have recently received an oral cholecystographic contrast agent.

7.2 Drug-Laboratory Test Interactions

Effect on Thyroid Tests

The results of protein bound iodine and radioactive iodine uptake studies, which depend on iodine estimation, will not accurately reflect thyroid function for at least 16 days following administration of iodinated contrast agents. However, thyroid function tests which do not depend on iodine estimations (e.g., T3 resin uptake and total or free thyroxine T4 assays) are not affected.

Effect on Urine Tests

As reported with other contrast agents, VISIPAQUE may produce a false-positive result for protein in the urine using urine dip tests. However, the Coomassie blue method has been shown to give accurate results for the measurement of urine protein in the presence of VISIPAQUE. In addition, care should be used in interpreting the results of urine specific gravity measurements in the presence of high levels of VISIPAQUE and other contrast agents in the urine. Refractometry or urine osmolality may be substituted.

8 USE IN SPECIFIC POPULATIONS

8.1 Pregnancy

Risk Summary

There are no data with iodixanol use in pregnant women to inform any drug-associated risks. In animal reproduction studies, no developmental toxicity occurred with intravenous iodixanol administration to rats and rabbits at doses up to 0.24 (rat) or 0.48 (rabbit) times the maximum recommended human intravenous dose (see Data).

All pregnancies have a background risk of birth defect, loss or other adverse outcomes. In the U.S. general population, the estimated background risk of major birth defects and miscarriage in clinically recognized pregnancies is 2 to 4% and 15 to 20%, respectively.

Data

Animal Data

Reproduction studies were performed in rats and rabbits with intravenous administration of iodixanol at doses up to 2 g Iodine/kg, daily, from implantation of the embryo (gestation day 7 in rat; 6 in rabbit) through closure of the hard palate (gestation day 17 in rats; 18 in rabbits). No maternal toxicity occurred, and no adverse effects occurred on fetal survival, embryo-fetal development, or the ability of dams to rear a litter.

8.2 Lactation

Risk Summary

There are no data on the presence of iodixanol in human milk, the effects on the breastfed infant or the effects on milk production. Iodinated contrast agents are poorly excreted into human milk and are poorly absorbed by the gastrointestinal tract of a breastfed infant. The developmental and health benefits of breastfeeding should be considered along with the mother's clinical need for VISIPAQUE and any potential adverse effects on the breastfed infant from VISIPAQUE or from the underlying maternal condition.

Clinical Considerations

Interruption of breastfeeding after exposure to iodinated contrast agents is not necessary because the potential exposure of the breastfed infant to iodine is small. However, a lactating woman may consider interrupting breastfeeding and pumping and discarding breast milk for 10 hours (approximately 5 elimination half-lives) after VISIPAQUE administration in order to minimize drug exposure to a breast fed infant.

8.4 Pediatric Use

The safety and efficacy of VISIPAQUE have been established in pediatric patients down to birth for angiocardiography, cerebral arteriography, visceral arteriography, CT imaging of the head and body, and excretory urography. The safety and efficacy of VISIPAQUE have also been established in pediatric patients 12 years and older for intra-arterial digital subtraction angiography, peripheral arteriography, peripheral venography and CCTA. Use of VISIPAQUE is supported by evidence from adequate and well controlled studies of VISIPAQUE in adults and additional safety data obtained in 459 pediatric patients. In general, the types of adverse reactions reported are similar to those of adults. A higher number of adverse events in patients less than 1 year of age compared to older patients were observed in a study of VISIPAQUE [see Adverse Events (6.3)]. The elimination of VISIPAQUE is slower in this age group [see Clinical Pharmacology (12.3)].

Thyroid function tests indicative of thyroid dysfunction, characterized by hypothyroidism or transient thyroid suppression have been reported following iodinated contrast media administration in pediatric patients, including term and preterm neonates. Some patients were treated for hypothyroidism. After exposure to iodinated contrast media, individualize thyroid function monitoring in pediatric patients 0 to 3 years of age based on underlying risk factors, especially in term and preterm neonates [see Warnings and Precautions (5.8) and Adverse Reactions (6.2)].

Pediatric patients at higher risk of experiencing an adverse reaction during and after administration of any contrast agent may include those with asthma, hypersensitivity to other medication and/or allergens, cyanotic and acyanotic heart disease, congestive heart failure, or a serum creatinine greater than 1.5 mg/dL. Pediatric patients with immature renal function or dehydration may be at increased risk for adverse events due to slower elimination of iodinated contrast agents [see Clinical Pharmacology (12.3)].

8.5 Geriatric Use

In clinical studies of VISIPAQUE, 254/757 (34%) of patients were 65 and over. No overall differences in safety or effectiveness were observed between these patients and younger patients. Other reported clinical experience has not identified differences in response between the elderly and younger patients, but greater sensitivity of some older individuals cannot be ruled out. In general, dose selection for an elderly patient should be cautious usually starting at the low end of the dosing range, reflecting the greater frequency of decreased hepatic, renal or cardiac function, and of concomitant disease or other drug therapy.

10 OVERDOSAGE

The adverse effects of overdosage of any contrast agent may be life-threatening and affect mainly the pulmonary and cardiovascular systems. Treatment of an overdosage is directed toward the support of all vital functions and prompt institution of symptomatic therapy. VISIPAQUE Injection does not bind to plasma or serum protein and can be dialyzed.

11 DESCRIPTION

11.1 Chemical Characteristics

VISIPAQUE (iodixanol) injection is a dimeric, iso-osmolar, nonionic, water-soluble, radiographic contrast medium for intravascular (intravenous and intra-arterial) use. It is provided as a ready-to-use sterile, pyrogen-free, and preservative free, colorless to pale yellow solution.

The chemical formula is 5,5´-[(2-hydroxy-1,3-propanediyl) bis(acetylimino)] bis[N,N´-bis(2,3-dihydroxypropyl)-2,4,6-triiodo- 1,3- benzenedicarboxamide] with a molecular weight of 1550.20 (iodine content 49.1%)

VISIPAQUE (C35H44I6N6O15) has the following structural formula:

VISIPAQUE is available in two strengths:

- VISIPAQUE 270 mg Iodine/mL (550 mg Iodixanol/mL), 0.074 mg calcium chloride dihydrate, 1.87 mg sodium chloride, 1.2 mg tromethamine, and 0.1 mg edetate calcium disodium.
- VISIPAQUE 320 mg Iodine/mL (652 mg Iodixanol/mL), 0.044 mg calcium chloride dihydrate, 1.11 mg sodium chloride, 1.2 mg tromethamine and 0.1 mg edetate calcium disodium.

Sodium chloride and calcium chloride have been added, resulting in an isotonic solution for injection providing for both concentrations a sodium/calcium ratio equivalent to blood.

The pH is adjusted to 7.4 with hydrochloric acid and/or sodium hydroxide to achieve a range between pH 6.8 and 7.7 at 22°C.

11.2 Physical Characteristics

The two concentrations of VISIPAQUE Injection (270 mg Iodine/mL and 320 mg Iodine/mL) have the following physical properties:

TABLE 4 Physical Properties of VISIPAQUE
Parameter |  | Concentration (mg Iodine/mL)
 |  | 320 | 270
Osmolality (mOsmol/kg water) |  | 290 | 290
Viscosity (cP) | @ 20°C | 26.6 | 12.7
 | @ 37°C | 11.8 | 6.3
Density (g/mL) | @ 20°C | 1.369 | 1.314
 | @ 37°C | 1.356 | 1.303

12 CLINICAL PHARMACOLOGY

12.1 Mechanism of Action

Intravascular injection of iodixanol opacifies vessels in the path of flow of the contrast agent, permitting visualization of internal structures.

In imaging of the body, iodinated contrast agents diffuse from the vascular into the extravascular space. In a normal brain with an intact blood-brain barrier, contrast does not diffuse into the extravascular space. In patients with a disrupted blood- brain barrier, contrast agent accumulates in the interstitial space in the region of disruption.

12.2 Pharmacodynamics

Following administration of VISIPAQUE, the degree of enhancement is directly related to the iodine content in an administered dose. Peak iodine plasma levels occur immediately following rapid injection. The time to maximum contrast enhancement can vary, depending on the organ, from the time that peak blood iodine concentrations are reached to one hour after intravenous bolus administration. When a delay between peak blood iodine concentrations and peak contrast is present, it suggests that radiographic contrast enhancement is at least in part dependent on the accumulation of iodine- containing medium within the lesion and outside the blood pool.

For angiography, contrast enhancement is greatest immediately (15 seconds to 120 seconds) after rapid injection. Iodinated contrast agents may be visualized in the renal parenchyma within 30 to 60 seconds following rapid intravenous injection. Opacification of the calyces and pelves in patients with normal renal function becomes apparent within 1 to 3 minutes, with optimum contrast occurring within 5 to 15 minutes.

12.3 Pharmacokinetics

Distribution

In an in vitro human plasma study, iodixanol did not bind to protein. The volume of distribution in adults was 0.26 L/kg body weight, consistent with distribution to extracellular space.

Elimination

In 40 healthy, young male volunteers receiving a single intravenous administration of VISIPAQUE in doses of 0.3 to 1.2 gram Iodine/kg body weight, the elimination half-life was 2.1 hr. (± 0.1). Renal clearance was 110 ± 14 mL/min, equivalent to glomerular filtration (108 mL/min). These values were independent of the dose administered.

Metabolism

Iodixanol does not undergo metabolism.

Excretion

In adults, approximately 97% of the injected dose of iodixanol is excreted unchanged in urine within 24 hours, with less than 2% excreted in feces within five days post-injection.

Specific Populations

Pediatric: Forty pediatric patients ≤12 years old, with renal function that is normal for their age, received multiple intra- arterial administrations of VISIPAQUE in doses of 0.32 to 3.2 gram Iodine/kg body weight. The elimination half-lives for these patients are shown in Table 5.

Dose adjustments to account for differences in elimination half-life in pediatric patients less than 6 months of age have not been studied.

TABLE 5 MEAN ELIMINATION HALF-LIFE* IN PEDIATRIC PATIENTS
Age Range | Number of Patients | Elimination half-life
 |  | (hr. ± SD)
Newborn to < 2 months | 8 | 4.1 ± 1.4
2 to 6 months | 8 | 2.8 ± 0.6
6 to 12 months | 9 | 2.4 ± 0.4
1 to 2 years | 5 | 2.3 ± 0.6
2 to 12 years | 10 | 2.3 ± 0.5
Adults | 40 | 2.1 ± 0.1

Renal Impairment: In patients with significantly impaired renal function, the total clearance of iodixanol is reduced and the half-life is increased. In a study of 16 adult patients who were scheduled for renal transplant, the mean creatinine clearance was 13.6 ± 4.7 mL/min). In these patients, plasma half-life was 23 hours (t1/2 for typical patients = 2.1 hours). Contrast enhancement time in kidneys increased from 6 hours to at least 24 hours. Dose adjustments in patients with renal impairment have not been studied. In patients with normal blood brain barriers and severe renal impairment, iodinated contrast agents have been associated with blood-brain barrier disruption and accumulation of contrast in the brain.

VISIPAQUE has been shown to be dialyzable. In an in vitro hemodialysis study, after 4 hours of dialysis with a cellulose membrane, approximately 36% of iodixanol was removed from the plasma. After 4 hours of dialysis with polysulfone membranes, approximately 49% of iodixanol was removed.

13 NONCLINICAL TOXICOLOGY

13.1 Carcinogenesis, Mutagenesis, Impairment of Fertility

Long-term animal studies have not been performed with iodixanol to evaluate carcinogenic potential. Iodixanol was not genotoxic in a series of studies including the Ames test, the CHO/HGPRT assay, a chromosome aberration assay in CHO cells, and a mouse micronucleus assay.

Iodixanol did not impair the fertility of male or female rats when administered at doses up to 0.24 times the maximum recommended human dose.

14 CLINICAL STUDIES

VISIPAQUE was studied in 1244 adult patients. Approximately one-half (590) of the VISIPAQUE patients were 60 years of age or older; the mean age was 56 years (range 18 to 90). A total of patients, 806 (65%) were male. The racial distribution was: Caucasian-85%, Black-12%, Oriental <1%, and other or unknown-3%.

A total of 1235 patients were evaluable for efficacy. Efficacy assessment was based on quality of the radiographic diagnostic visualization (i.e., either: excellent, good, poor, or none) and on the ability to make a diagnosis (i.e., either: confirmed a previous diagnosis, found normal, or diagnosed new findings).

14.1 Intra-arterial Administration Studies

Angiocardiography, cerebral arteriography, peripheral arteriography, and visceral arteriography were studied with either one or both concentrations of VISIPAQUE Injection (270 mg Iodine/mL or 320 mg Iodine/mL). In these intra-arterial studies, diagnostic visualization ratings were good or excellent in all the patients and a radiologic diagnosis was made in all of the patients. In additional intra-arterial studies, overall quality of diagnostic visualization was rated optimal in the majority of patients and a radiologic diagnosis was made in all (100%) of the patients. The number of patients studied in each indication is provided below.

Angiocardiography was evaluated in two randomized, double-blind clinical studies in 101 adult patients given VISIPAQUE 320 mg Iodine/mL. Seven additional angiocardiography studies were performed in 217 adult patients given VISIPAQUE 320 mg Iodine/mL. Visualization ratings were good or excellent in all the patients given VISIPAQUE; a radiologic diagnosis was made in the majority of the patients. Confirmation of the radiologic findings by other diagnostic methods was not obtained.

Cerebral arteriography was evaluated in two randomized, double-blind clinical trials in 51 adult patients given VISIPAQUE 320 mg Iodine/mL. Two additional cerebral arteriography studies were performed in 15 adult patients given VISIPAQUE Injection 270 mg Iodine/mL, 40 patients given VISIPAQUE 320 mg Iodine/mL. Visualization ratings were good or excellent in all the patients a radiologic diagnosis was made in the majority of the patients. Confirmation of the radiologic findings by other diagnostic methods was not obtained.

Peripheral arteriography was evaluated in two randomized, double-blind clinical trials in 49 adult patients given VISIPAQUE 320 mg Iodine/mL. Four additional peripheral arteriography studies were performed in 41 adult patients given VISIPAQUE 270 mg Iodine/mL, 85 patients given VISIPAQUE 320 mg Iodine/mL. Visualization ratings were good or excellent in 100% of the patients given VISIPAQUE; a radiologic diagnosis was made in the majority of the patients. Confirmation of the radiologic findings by other diagnostic methods was not obtained.

Visceral arteriography was evaluated in two randomized, double-blind clinical trials in 55 adult patients given VISIPAQUE 320 mg Iodine/mL. Visualization ratings were good or excellent in all of the patients; a radiologic diagnosis was made in the majority of the patients. Confirmation of the radiologic findings by other diagnostic methods was not obtained.

Similar studies with digital subtraction angiography (DSA) were completed with comparable findings noted in cerebral arteriography, peripheral arteriography, and visceral arteriography. Studies have not been conducted to determine the lowest effective concentration of VISIPAQUE.

14.2 Intravenous Administration Studies

Excretory urography, computed tomography (CT) of the head, CT of the body, peripheral venography, and coronary computed tomography angiography (CCTA) were studied with either one or both VISIPAQUE Injection concentrations (270 mg Iodine/mL or 320 mg Iodine/mL). In the non-CCTA intravenous studies, diagnostic visualization ratings were good or excellent in 96 to 100% of the patients and a radiologic diagnosis was made in all of the patients given VISIPAQUE.

In the CCTA studies results were computed in terms of sensitivity and specificity compared to a standard of reference. The number of patients studied in each indication is provided below.

Excretory urography was evaluated in one uncontrolled, unblinded clinical trial in 40 patients, 20 given VISIPAQUE 270 mg Iodine/mL and 20 given VISIPAQUE 320 mg Iodine/mL, and in two randomized, double-blind clinical trials in 50 adult patients given VISIPAQUE 270 mg Iodine/mL, 50 patients given VISIPAQUE 320 mg Iodine/mL. Visualization ratings were good or excellent in all of the patients given VISIPAQUE; a radiologic diagnosis was made in the majority of the patients. Confirmation of the radiologic findings by other diagnostic methods was not obtained.

CT of the head was evaluated in two randomized, double-blind clinical trials in 49 adult patients given VISIPAQUE 270 mg Iodine/mL, in 50 patients given VISIPAQUE 320 mg Iodine/mL. CT of the body was evaluated in three randomized, double-blind clinical trials in 104 adult patients given VISIPAQUE 270 mg Iodine/mL, and 109 patients given VISIPAQUE 320 mg Iodine/mL. In both CT of the head and body, visualization ratings were good or excellent in all of the patients given VISIPAQUE; a radiologic diagnosis was made in the majority of the patients. Confirmation of the radiologic findings by other diagnostic methods was not obtained.

Peripheral venography was evaluated in two randomized, double-blind clinical studies in 46 adult patients given VISIPAQUE 270 mg Iodine/mL. Visualization ratings were good or excellent in all of the patients given VISIPAQUE; a radiologic diagnosis was made in the majority of the patients. The results were similar to those of the active control. Confirmation of the radiologic findings by other diagnostic methods was not obtained.

VISIPAQUE 320 mg Iodine/mL for CCTA was evaluated in two prospective, multicenter clinical studies in a total of 1106 adult patients. The patient population consisted of stable outpatients with chest pain or other symptoms suggestive of coronary artery disease, and no known history of coronary disease. All the CCTAs were done using 64 detector row CT scanners. Most of the patients received beta-blocker medication for heart rate control and nitroglycerin for vasodilation. Patients with irregular cardiac rhythm or heart rate above 100 beats per minute were excluded. The mean patient age was 57 years in the first study and 59 years in the second study. Both studies had more men than women (59% male in the first study and 51% male in the second study), and more Caucasian patients (88% in the first study and 78% in the second study) than Black, Asian, or other patients. The BMI range was 17 to 50 with a mean of 31 in the first study and a BMI range of 15 to 71 with a mean of 30 in the second study.

In the first study, 230 patients (906 vessels) were evaluable for efficacy using the reference standard of invasive coronary angiography. Seventy-five vessels (8%, in 49 patients) were evaluated as positive for ≥ 50% stenosis. The CCTA images were randomized and read by three blinded, independent readers; the coronary angiography images were interpreted by an independent, blinded reader. Assuming independence between vessels, the vessel-level sensitivity (95% CI) for assessing ≥ 50% stenosis was 76% (63, 86) for reader 1, 89% (79, 95) for reader 2 and 77% (65, 86) for reader 3. The vessel-level specificity (95% CI) was 85% (81, 89) for reader 1, 84% (81, 87) for reader 2, and 89% (86, 91) for reader 3. The vessel-level sensitivity and specificity for assessing ≥ 70% stenosis were similar.

In a second study, 857 patients were evaluable for efficacy. Patients were followed up for 12 months after CCTA and the reference standard was a composite of pre-specified clinical outcomes (death, major adverse cardiac event, or coronary revascularization). Seventy-six patients (9%) experienced one or more of the pre-specified outcomes over 12 months of follow-up. The sensitivity (95% CI) and specificity (95% CI) of a positive CCTA finding (≥ 50% stenosis at the patient level) to predict one or more of the pre-specified clinical outcomes was 95% (87, 99) and 87% (84, 89), respectively.

16 HOW SUPPLIED/STORAGE AND HANDLING

16.1 How supplied

VISIPAQUE injection is a ready-to-use sterile, pyrogen-free, preservative free, colorless to pale yellow solution available in two (2) strengths. It is supplied in the following configurations:

PHARMACY BULK PACKAGE CONTAINING VISIPAQUE (iodixanol) Injection 320 mg Iodine/mL:

500 mL in multiple-dose +PLUSPAK™ (polymer bottle), boxes of 10 | (NDC 0407-2223-23)

SINGLE-DOSE BOTTLE CONTAINING VISIPAQUE (iodixanol) Injection 270 mg Iodine/mL:

50 mL in single-dose +PLUSPAK™ (polymer bottle), boxes of 10 | (NDC 0407-2222-16)
100 mL in single-dose +PLUSPAK™ (polymer bottle), boxes of 10 | (NDC 0407-2222-17)
150 mL in single-dose +PLUSPAK™ (polymer bottle), boxes of 10 | (NDC 0407-2222-19)
200 mL in single-dose +PLUSPAK™ (polymer bottle), boxes of 10 | (NDC 0407-2222-21)

16.2 Storage and Handling

Protect VISIPAQUE from direct exposure to sunlight.

Store VISIPAQUE at controlled room temperature, 20°C to 25°C (68°F to 77°F); excursions permitted to 15°C to 30°C (59°F to 86°F) [see USP Controlled Room Temperature].

VISIPAQUE may be stored in a contrast media warmer for up to one month at 37°C (98.6°F).

Do not freeze. Discard any product that is inadvertently frozen, as freezing may compromise the closure integrity of the immediate container.

DIRECTIONS FOR PROPER USE OF VISIPAQUE PHARMACY BULK PACKAGE

- Restrict the transfer of VISIPAQUE (iodixanol) Injection from the Pharmacy Bulk Package to a suitable work area, such as a laminar flow hood.
- Penetrate the container closure only one time, utilizing a suitable transfer device and aseptic technique.
- Perform the withdrawal of container contents without delay. However, a maximum time of 8 hours from initial closure entry is permitted to complete fluid transfer operations. Do not remove the container from the aseptic area during the entire 8-hour period.
- After the closure has been entered, the temperature of the container should not exceed 37°C.

17 PATIENT COUNSELING INFORMATION

Hypersensitivity Reactions

Advise the patient concerning the risk of hypersensitivity reactions that can occur both during and after VISIPAQUE administration. Advise the patient to report any signs or symptoms of hypersensitivity reactions during the procedure and to seek immediate medical attention for any signs or symptoms experienced after discharge [see Warnings and Precautions (5.2)].

Advise patients to inform their physician if they develop a rash after receiving VISIPAQUE [see Warnings and Precautions (5.11)].

Contrast-Induced Acute Kidney Injury

Advise the patient concerning appropriate hydration to decrease the risk of contrast-induced acute kidney injury [see Warnings and Precautions (5.3)].

Extravasation

If extravasation occurs during injection, advise patients to seek medical care for progression of symptoms [see Warnings and Precautions (5.6)].

Thyroid Dysfunction

Advise parents/caregivers about the risk of developing thyroid dysfunction after VISIPAQUE administration. Advise parents/caregivers about when to seek medical care for their child to monitor for thyroid dysfunction [see Warnings and Precautions (5.8)].

Distributed by GE Healthcare Inc.,
Arlington Heights, IL 60004 U.S.A.

Product of Norwegian Origin.

VISIPAQUE is a trademark of GE HealthCare or one of its subsidiaries.

GE is a trademark of General Electric Company used under trademark license.

© 2025 GE HealthCare

PRINCIPAL DISPLAY PANEL - 500 mL Bottle Box Label

NDC 0407-2223-23

V-568B

Contains
10 x 500 mL
Bottles

VISIPAQUE™
(iodixanol) Injection

320 mgI/mL

PHARMACY BULK PACKAGE
Not for Direct Infusion

NOT FOR INTRATHECAL USE

in +PLUSPAK™ (polymer bottle)

Multi-Dose Bottle
Sterile Aqueous Injection

Each 1 mL contains 652 mg of iodixanol (320 mg organically bound iodine),
0.044 mg calcium chloride dihydrate, 1.11 mg sodium chloride,
1.2 mg tromethamine, and 0.1 mg edetate calcium disodium.
The pH is adjusted to 7.4 with hydrochloric acid and/or sodium hydroxide
to achieve a range between pH 6.8-7.7. Osmolality is 290 mOsm/kg water.
No preservative added. Once a sterile transfer needle or spike has been
inserted into the container outlet site, withdrawal of container contents
should be completed without delay. If fluid transfer cannot be completed
without delay, discard the container no later than 8 hours after initial puncture.
Protect from light. Store at 20°-25°C (68°-77°F); excursions permitted to
15°-30°C (59°-86°F) [see USP]. Do not freeze. For indications, dosage and further
information on the use of the Pharmacy Bulk Package,
see prescribing information.
Rx ONLY

Distributed by GE Healthcare Inc.,
Arlington Heights, IL 60004 U.S.A.
For inquiries call 1-800-654-0118

Product of Norwegian Origin.

(01) 20304072223232

Exp.:

Lot:

1209204 USA GE HealthCare